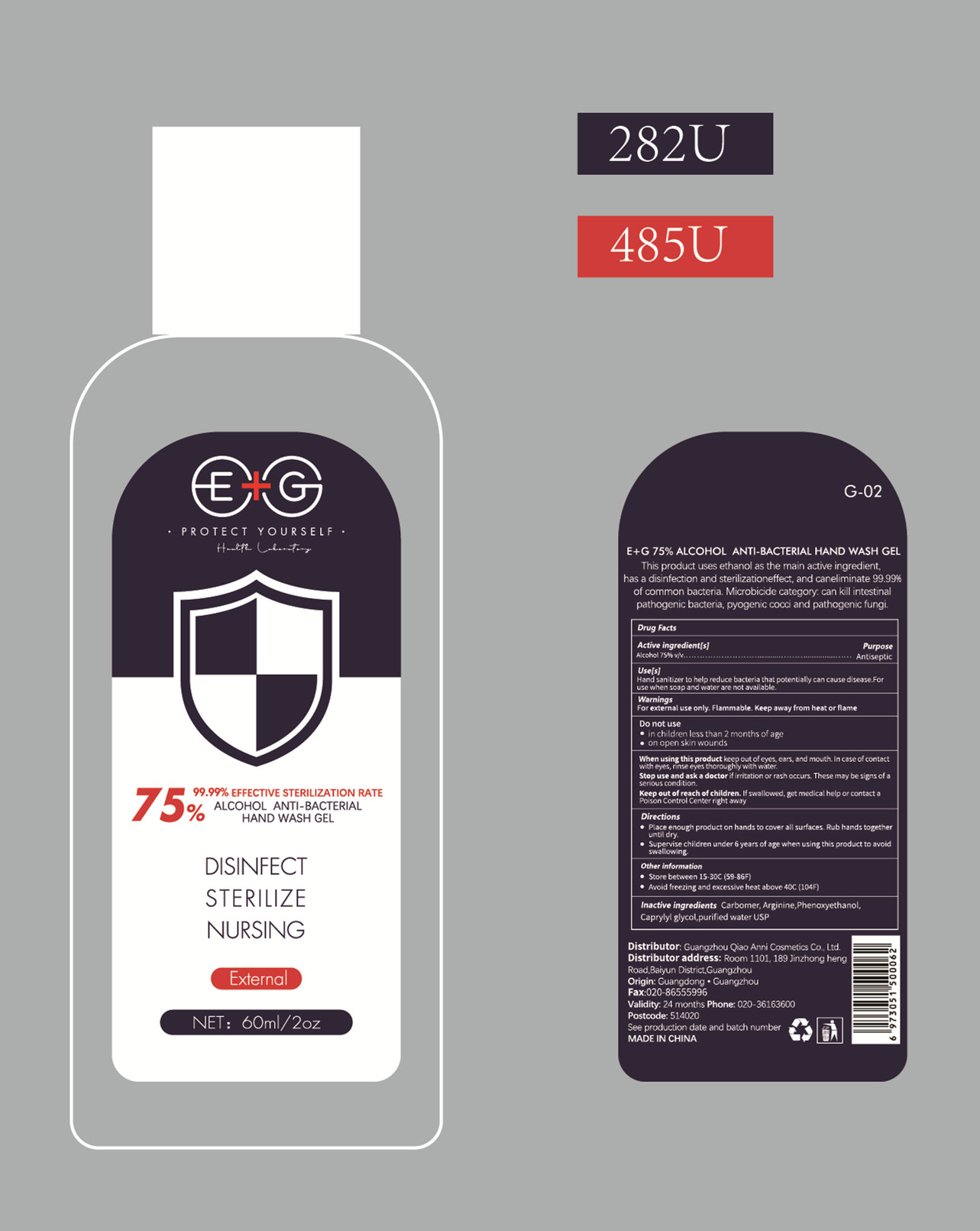 DRUG LABEL: E G 75% ALCOHOL ANTI-BACTERIAL HAND WASHGEL
NDC: 68923-002 | Form: GEL
Manufacturer: Guangzhou Qiao Anni Cosmetics Co., Ltd.
Category: otc | Type: HUMAN OTC DRUG LABEL
Date: 20200608

ACTIVE INGREDIENTS: ALCOHOL 45 mL/60 mL
INACTIVE INGREDIENTS: CARBOMER HOMOPOLYMER, UNSPECIFIED TYPE; ARGININE; CAPRYLYL GLYCOL; WATER; PHENOXYETHANOL

DOSAGE AND ADMINISTRATION

1.Store between 15-30°C (59-86°F)
2.Awoid freezing and excessive heat above 40°C (104°F)

INACTIVE INGREDIENT

Carbomer， Arginine，Phenoxyethanol, Caprylyl glycol, purified water USP

INDICATIONS AND USAGE

1.Place enough product on hands to cover all surfaces. Rub hands together until dry.
2.Supervise children under 6 years of age when using this product to avoid swallowing.

ACTIVE INGREDIENT

alcohol

keep out of reach of children

PURPOSE

Disinfection
Sterilization
No Rinseing

WARNINGS

For external use only. Flammable. Keep away from heat or flame